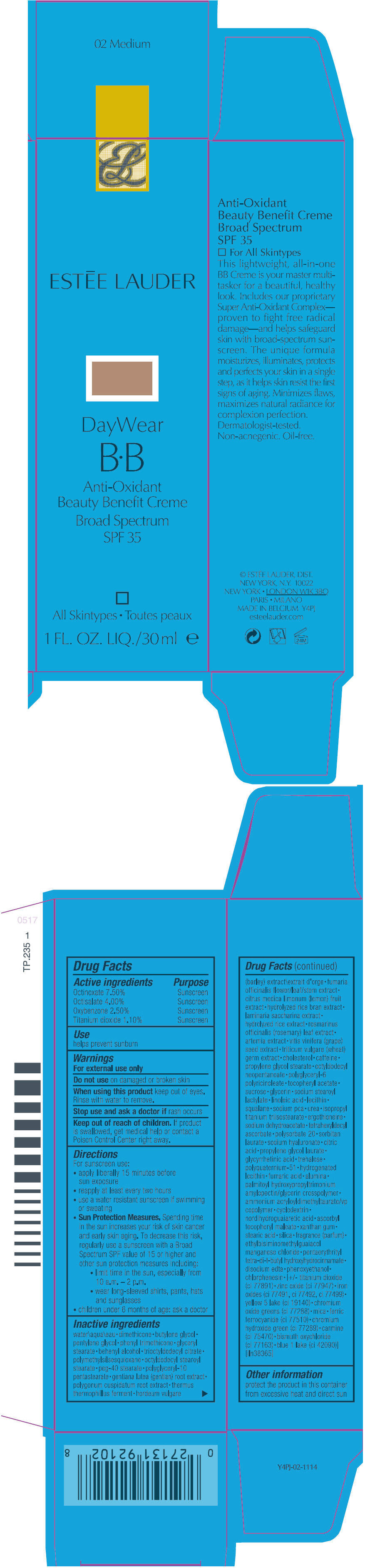 DRUG LABEL: DAYWEAR BB 
NDC: 11559-015 | Form: CREAM
Manufacturer: ESTEE LAUDER INC
Category: otc | Type: HUMAN OTC DRUG LABEL
Date: 20120406

ACTIVE INGREDIENTS: OCTINOXATE 7.5 mL/100 mL; OCTISALATE 4 mL/100 mL; OXYBENZONE 2.5 mL/100 mL; TITANIUM DIOXIDE 1.1 mL/100 mL
INACTIVE INGREDIENTS: WATER; DIMETHICONE; BUTYLENE GLYCOL; PENTYLENE GLYCOL; PHENYL TRIMETHICONE; GLYCERYL MONOSTEARATE; DOCOSANOL; OCTYLDODECYL STEAROYL STEARATE; PEG-40 STEARATE; GENTIANA LUTEA ROOT; POLYGONUM CUSPIDATUM ROOT; HORDEUM VULGARE ROOT; FUMARIA OFFICINALIS FLOWERING TOP; LEMON; SACCHARINA LATISSIMA THALLUS; ROSEMARY; VITIS VINIFERA SEED; WHEAT GERM; CHOLESTEROL; CAFFEINE; PROPYLENE GLYCOL STEARATE; OCTYLDODECYL NEOPENTANOATE; ALPHA-TOCOPHEROL ACETATE; SUCROSE; GLYCERIN; SODIUM STEAROYL LACTYLATE; LINOLEIC ACID; SQUALANE; SODIUM PYRROLIDONE CARBOXYLATE; UREA; ERGOTHIONEINE; SODIUM DEHYDROACETATE; TETRAHEXYLDECYL ASCORBATE; POLYSORBATE 20; SORBITAN MONOLAURATE; HYALURONATE SODIUM; CITRIC ACID MONOHYDRATE; PROPYLENE GLYCOL LAURATES; ENOXOLONE; TREHALOSE; FUMARIC ACID; ALUMINUM OXIDE; MASOPROCOL; XANTHAN GUM; STEARIC ACID; SILICON DIOXIDE; EDETATE DISODIUM; PHENOXYETHANOL; CHLORPHENESIN; ZINC OXIDE; FERRIC OXIDE RED; FERRIC OXIDE YELLOW; FERROSOFERRIC OXIDE; FD&C YELLOW NO. 5; CHROMIC OXIDE; MICA; FERRIC FERROCYANIDE; COCHINEAL; BISMUTH OXYCHLORIDE; FD&C BLUE NO. 1

ESTĒE LAUDER
DayWear B☁B Anti-Oxidant Beauty Broad Spectrum Benefit Creme

Drug Facts

ACTIVE INGREDIENT

Active ingredients | Purpose
Octinoxate 7.50% | Sunscreen
Octisalate 4.00% | Sunscreen
Oxybenzone 2.50% | Sunscreen
Titanium dioxide 1.10% | Sunscreen

Use

helps prevent sunburn

Warnings

For external use only

Do not use on damaged or broken skin

When using this product keep out of eyes. Rinse with water to remove.

Stop use and ask a doctor if rash occurs

Keep out of reach of children. If product is swallowed, get medical help or contact a Poison Control Center right away.

Directions

For sunscreen use:

- apply liberally 15 minutes before sun exposure
- reapply at least every two hours
- use a water resistant sunscreen if swimming or sweating
- Sun Protection Measures. Spending time in the sun increases your risk of skin cancer and early skin aging. To decrease this risk, regularly use a sunscreen with a Broad Spectrum SPF value of 15 or higher and other sun protection measures including:
  - limit time in the sun, especially from 10 a.m. – 2 p.m.
  - wear long-sleeved shirts, pants, hats and sunglasses
- children under 6 months of age: ask a doctor

Inactive ingredients

water\aqua\eau • dimethicone • butylene glycol • pentylene glycol • phenyl trimethicone • glyceryl stearate • behenyl alcohol • trioctyldodecyl citrate • polymethylsilsesquioxane • octyldodecyl stearoyl stearate • peg-40 stearate • polyglyceryl-10 pentastearate • gentiana lutea (gentian) root extract • polygonum cuspidatum root extract • thermus thermophillus ferment • hordeum vulgare (barley) extract\extrait d' orge • fumaria officinalis flower/leaf/stem extract • citrus medica limonum (lemon) fruit extract • hydrolyzed rice bran extract • laminaria saccharina extract • hydrolyzed rice extract • rosmarinus officinalis (rosemary) leaf extract • artemia extract • vitis vinifera (grape) seed extract • triticum vulgare (wheat) germ extract • cholesterol • caffeine • propylene glycol stearate • octyldodecyl neopentanoate • polyglyceryl-6 polyricinoleate • tocopheryl acetate • sucrose • glycerin • sodium stearoyl lactylate • linoleic acid • lecithin • squalane • sodium pca • urea • isopropyl titanium triisostearate • ergothioneine • sodium dehydroacetate • tetrahexyldecyl ascorbate • polysorbate 20 • sorbitan laurate • sodium hyaluronate • citric acid • propylene glycol laurate • glycyrrhetinic acid • trehalose • polyquaternium-51 • hydrogenated lecithin • fumaric acid • alumina • palmitoyl hydroxypropyltrimonium amylopectin/glycerin crosspolymer • ammonium acryloyldimethyltaurate/vp copolymer • cyclodextrin • nordihydroguaiaretic acid • ascorbyl tocopheryl maleate • xanthan gum • stearic acid • silica • fragrance (parfum) • ethylbisiminomethylguaiacol manganese chloride • pentaerythrityl tetra-di-t-butyl hydroxyhydrocinnamate • disodium edta • phenoxyethanol • chlorphenesin • [+/- titanium dioxide (ci 77891) • zinc oxide (ci 77947) • iron oxides (ci 77491, ci 77492, ci 77499) • yellow 5 lake (ci 19140) • chromium oxide greens (ci 77288) • mica • ferric ferrocyanide (ci 77510) • chromium hydroxide green (ci 77289) • carmine (ci 75470) • bismuth oxychloride (ci 77163) • blue 1 lake (ci 42090)] [iln38365]

Other information

protect the product in this container from excessive heat and direct sun

© ESTĒE LAUDER, DIST.
NEW YORK, N.Y. 10022

PRINCIPAL DISPLAY PANEL - 30 ml Carton

ESTĒE LAUDER

DayWear

B•B

Anti-Oxidant
Beauty Benefit Creme
Broad Spectrum
SPF 35

All Skintypes

1 FL. OZ. LIQ./30 ml e